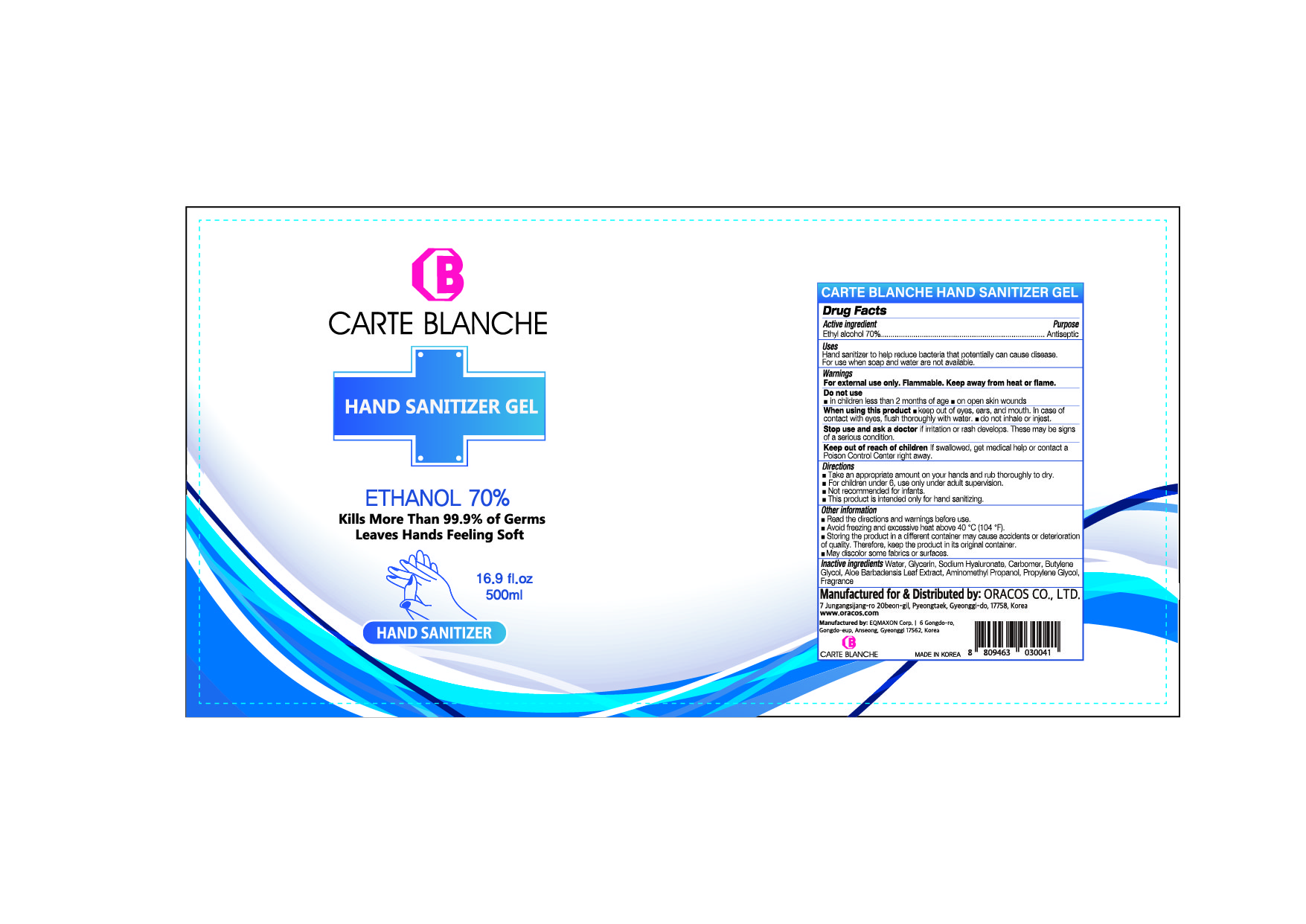 DRUG LABEL: CARTE BLANCHE HAND SANIZITER Gel
NDC: 75201-500 | Form: GEL
Manufacturer: ORACOS CO LTD.
Category: otc | Type: HUMAN OTC DRUG LABEL
Date: 20201028

ACTIVE INGREDIENTS: ALCOHOL 350 mL/500 mL
INACTIVE INGREDIENTS: GLYCERIN; WATER; ALOE VERA LEAF; PROPYLENE GLYCOL; HYALURONATE SODIUM; BUTYLENE GLYCOL; CARBOMER HOMOPOLYMER, UNSPECIFIED TYPE; AMINOMETHYLPROPANOL

75201-500-01 CARTE BLANCHE HAND SANIZITER GEL